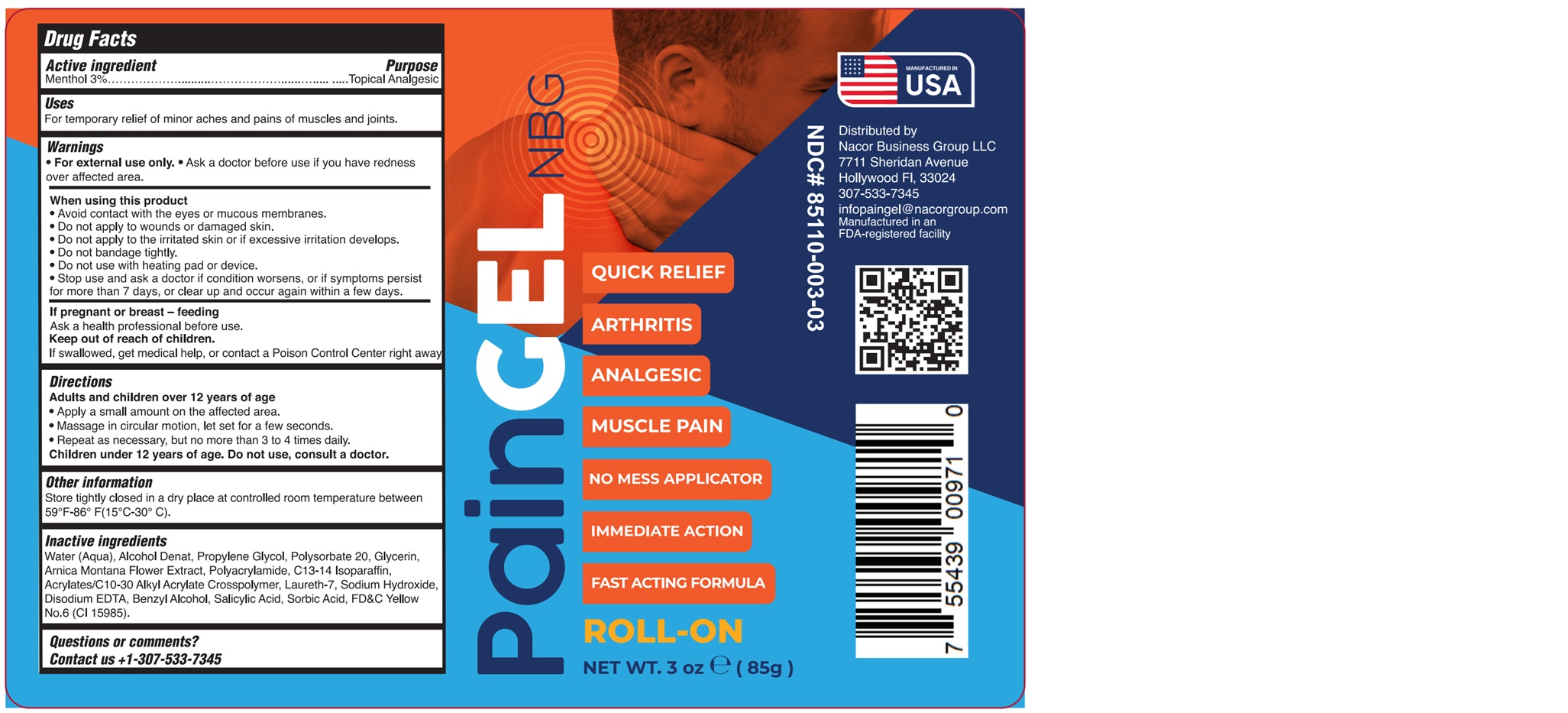 DRUG LABEL: PAINGEL ROLL-ON
NDC: 85110-003 | Form: GEL
Manufacturer: NACOR BUSINESS GROUP LLC
Category: otc | Type: HUMAN OTC DRUG LABEL
Date: 20251106

ACTIVE INGREDIENTS: MENTHOL 3 g/100 g
INACTIVE INGREDIENTS: WATER; ALCOHOL; PROPYLENE GLYCOL; POLYSORBATE 20; GLYCERIN; ARNICA MONTANA FLOWER; POLYACRYLAMIDE (1500 MW); C13-14 ISOPARAFFIN; ACRYLATES/C10-30 ALKYL ACRYLATE CROSSPOLYMER (60000 MPA.S AT 1.0%); LAURETH-7; SODIUM HYDROXIDE; EDETATE DISODIUM; BENZYL ALCOHOL; SALICYLIC ACID; SORBIC ACID; FD&C YELLOW NO. 6

85110-003-03

ACTIVE INGREDIENT

Menthol ………………………………...…………………………….…. 3%

PURPOSE

Topical Analgesic

Uses

For temporary relief of minor aches and pains in muscles and joints.

WARNINGS

• For external use only.

• Ask a doctor before use if you have redness over affected area.

WHEN USING

• Avoid contact with the eyes or mucous membranes.
• Do not apply to wounds or damaged skin.
• Do not apply to the irritated skin or if excessive irritation develops.
• Do not bandage tightly.
• Do not use with heating pad or device.
• Stop use and ask a doctor if condition worsens, or if symptoms persist for more than 7 days, or clear up and occur again within a few days.

If pregnant or breast-feeding

Ask a health professional before use.

KEEP OUT OF REACH OF CHILDREN

If swallowed, get medical help or contact a Poison Control Center right away.

Directions

Adults and children over 12 years of age

• Apply a small amount on the affected area.

• Massage in circular motion, let set for a few seconds.

• Repeat as necessary, but no more than 3 to 4 times daily.

Children under 12 years of age. Do not use, consult a doctor.

Other information

Store tightly closed in a dry place at controlled room temperature between 59°F-86° F(15°C-30° C).

INACTIVE INGREDIENT

Water (Aqua), Alcohol Denat, Propylene Glycol, Polysorbate 20, Glycerin, Arnica Montana Flower Extract, Polyacrylamide, C13-14 Isoparaffin, Acrylates/C10-30 Alkyl Acrylate Crosspolymer, Laureth-7, Sodium Hydroxide, Disodium EDTA, Benzyl Alcohol, Salicylic Acid, Sorbic Acid, FD&C Yellow No.6 (CI 15985).

Questions or comments?

Contact us +1-307-533-7345